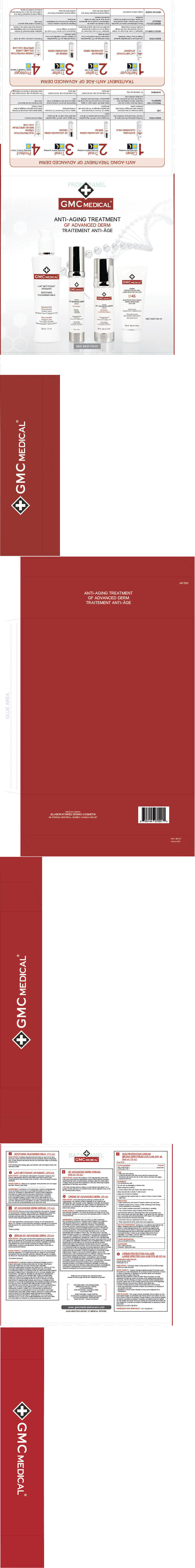 DRUG LABEL: GMC Medical
NDC: 64127-174 | Form: KIT | Route: TOPICAL
Manufacturer: Laboratoires dermo Cosmetik Inc
Category: otc | Type: HUMAN OTC DRUG LABEL
Date: 20140203

ACTIVE INGREDIENTS: zinc oxide 11.6 mg/100 mL; octinoxate 8.3 mg/100 mL
INACTIVE INGREDIENTS: WATER; CYCLOMETHICONE; DIMETHICONE; PHENYL TRIMETHICONE; HIGH DENSITY POLYETHYLENE; PPG-3 MYRISTYL ETHER; MICA; SILICON DIOXIDE; POLYGLYCERYL-10 DECAOLEATE; GLYCERIN; ISODODECANE; HECTORITE; PROPYLENE CARBONATE; POLYGONUM AVICULARE TOP; SENNA ALATA LEAF; PANTHENOL; .ALPHA.-TOCOPHEROL ACETATE; TRIETHOXYCAPRYLYLSILANE; PHENOXYETHANOL; ETHYLHEXYLGLYCERIN

GMC Medical®

Drug Facts

Active ingredients

Zinc oxide 10.5%
Octinoxate 7.5%

Purpose

Sunscreen

Uses

- Helps prevent sunburn.
- If used as directed with other sun protection measures (see Directions), decreases the risk of skin cancer and early skin aging caused by the sun.

WARNINGS

For external use only

Do not use on damaged or broken skin

When using this product:

- Avoid contact with eyes. Rinse with water to remove.

Stop use and ask a doctor if rash occurs

Keep out of reach of children.

- If swallowed, get medical help or contact a Poison Control Center right away.

DIRECTIONS

- Apply generously and evenly 15 minutes before sun exposure.
- Reapply at least every 2 hours, or after swimming, towel drying, heavy perspiration or showering.
- Use a water-resistant sunscreen if swimming or sweating.
- Ask a doctor before using on infants under 6 months.

Sun Protection Measures. Spending time in the sun increases your risk of skin cancer and early skin aging. To decrease the risk, regularly use a sunscreen with a Broad Spectrum SPF value of 15 or higher and other sun protection measures including:

- Limit time in the sun, especially from 10 a.m. – 2 p.m.
- Wear long-sleeved shirts, pants, hats and sunglasses.

INACTIVE INGREDIENTS

WATER/EAU, CYCLOMETHICONE, DIMETHICONE, PHENYL TRIMETHICONE, POLYETHYLENE, PPG-3 MYRISTYL ETHER, PPG-3 MYRISTYL ETHER NEOHEPTANOATE, CETYL PEG/PPG-10/1 DIMETHICONE, MICA, SILICA, POLYGLYCERYL-10 DECAOLEATE, GLYCERIN, ISODODECANE, DISTEARDIMONIUM, HECTORITE, PROPYLENE CARBONATE, POLYGONUM AVICULARE EXTRACT, CASSIA ALATA (CANDLE TREE) LEAF EXTRACT, PANTHENOL, TOCOPHERYL ACETATE, TRIETHOXYCAPRYLYLSILANE, PHENOXYETHANOL, ETHYLHEXYLGLYCERIN

OTHER INFORMATION

Store at 59-86°F (15-30°C).

QUESTIONS?

USA: 1 (800) 341-1531
CANADA: 1 (800) 361-1263

PRINCIPAL DISPLAY PANEL - Kit Carton

GMC MEDICAL®

ANTI-AGING TREATMENT
GF ADVANCED DERM

NDC 64127-134-01

NDC 64127-174-01